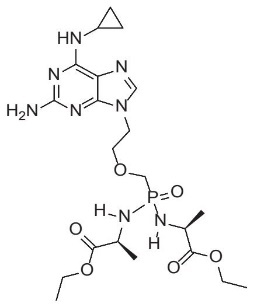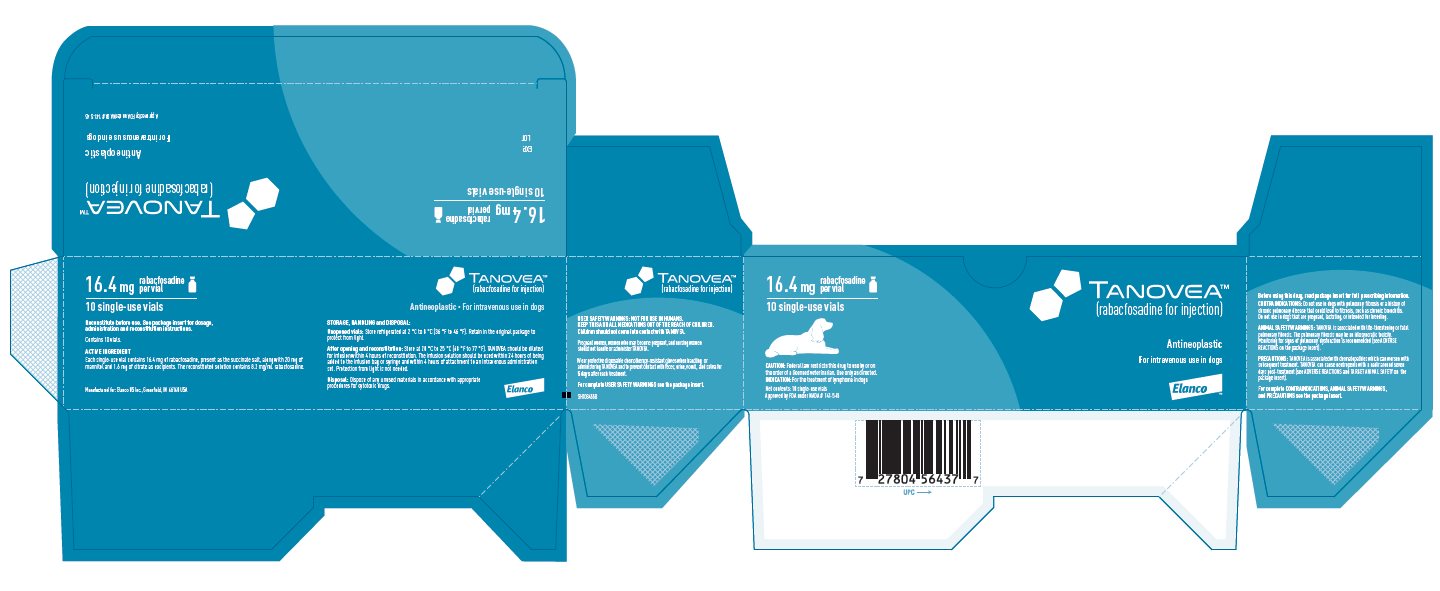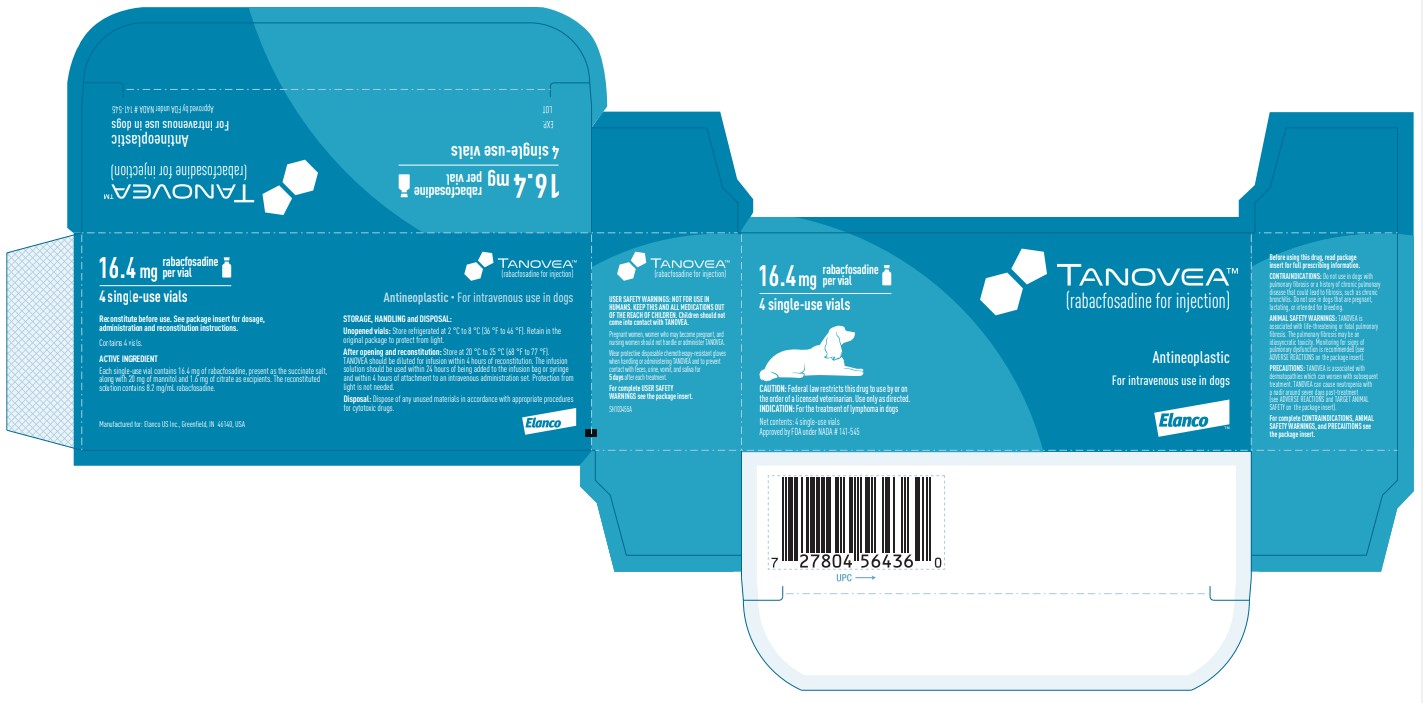 DRUG LABEL: Tanovea
NDC: 58198-0077 | Form: INJECTION, POWDER, FOR SOLUTION
Manufacturer: Elanco US Inc.
Category: animal | Type: PRESCRIPTION ANIMAL DRUG LABEL
Date: 20230117

ACTIVE INGREDIENTS: RABACFOSADINE SUCCINATE 16.4 mg/1 1

TANOVEATM

(rabacfosadine for injection)

16.4 mg rabacfosadine per vial

Antineoplastic

For intravenous use in dogs only

Approved by FDA under NADA # 141-545

CAUTION: Federal law restricts this drug to use by or on the order of a licensed veterinarian. Use only as directed.

DESCRIPTION:

TANOVEA (rabacfosadine for injection) is an acyclic nucleotide phosphonate. The molecular weight of rabacfosadine is 526.5 g/mole. The empirical formula is C21H35N8O6P. The structural formula is:

TANOVEA is supplied as a sterile, white to off-white lyophilized powder in the form of a cake contained in a 3 mL amber glass vial. Each single-use vial contains 16.4 mg of rabacfosadine, present as the succinate salt, along with 20 mg of mannitol and 1.6 mg of citrate as excipients.

INDICATION:

TANOVEA is indicated for the treatment of lymphoma in dogs.

DOSAGE AND ADMINISTRATION:

Always provide the Client Information Sheet to the dog owner with each dose administration.

Administer TANOVEA at 1 mg/kg body weight as a 30-minute intravenous infusion, once every three weeks, for up to five doses.

Stepwise dose reductions to 0.8 mg/kg and 0.66 mg/kg or dose delays may be used to manage adverse reactions.

TANOVEA is supplied as a sterile lyophilized powder for reconstitution before use. After reconstitution with 2 mL of 0.9% Sodium Chloride Injection, USP, the reconstituted solution contains 8.2 mg/mL of rabacfosadine.

Reconstitution and administration of TANOVEA

Wear chemotherapy-resistant gloves, goggles, and protective clothing in the preparation and administration of TANOVEA. Use aseptic technique in the preparation and administration of TANOVEA.

Reconstitution instructions

1. Obtain the desired number of vials from the refrigerator.
2. Add 2 mL of 0.9% Sodium Chloride Injection, USP to the single-use vial.
3. Gently invert the vial several times until the drug has completely dissolved and the solution is particle free.
4. The solution should be clear without visible particulates. If particulates are observed, the solution should be discarded.

Dilution for infusion and administration instructions

1. TANOVEA should be diluted for infusion within 4 hours of reconstitution.
2. Add the calculated volume of reconstituted TANOVEA (8.2 mg/mL) to 0.9% Sodium Chloride Injection, USP in a polyvinyl chloride (PVC) infusion bag or polypropylene infusion syringe to yield a total infusion volume of 2 mL/kg.
3. The volume of reconstituted TANOVEA should be calculated based on the exact weight of the dog. (See Table 1. for example doses and administration volumes).
4. The infusion solution should be used within 24 hours of being added to the infusion bag or syringe and within 4 hours of being added to an intravenous transfer set. Protection from light is not needed.
5. Administer TANOVEA as a 30-minute intravenous infusion.

Table 1. Example doses and volumes at 1 mg/kg.
Dog weight (kg) | Dog weight (lb) | Dose (mg) | Volume of reconstituted TANOVEA solution (mL) | Volume 0.9% NaCl (mL) | Total infusion volume (mL) | Rate of infusion (mL/minute)
5a | 11 | 5 | 0.6 | 9.4 | 10 | 0.3
10 | 22 | 10 | 1.2 | 18.8 | 20 | 0.7
15 | 33 | 15 | 1.8 | 28.2 | 30 | 1.0
20 | 44 | 20 | 2.4 | 37.6 | 40 | 1.3
25 | 55 | 25 | 3.0 | 47.0 | 50 | 1.7
30 | 66 | 30 | 3.7 | 56.3 | 60 | 2.0
35 | 77 | 35 | 4.3 | 65.7 | 70 | 2.3
40a | 88 | 40 | 4.9 | 75.1 | 80 | 2.7
a TANOVEA can be administered to dogs less than 5 kg and greater than 40 kg. Always calculate the dose based on the exact weight of the dog.

Compatibility of administration sets containing ethyl vinyl acetate (EVA) has not been evaluated.

CONTRAINDICATIONS:

Do not use in dogs with pulmonary fibrosis or a history of chronic pulmonary disease that could lead to fibrosis, such as chronic bronchitis (see WARNINGS). Do not use in West Highland White Terriers due to a genetic predisposition for development of pulmonary fibrosis. Use with caution in other terrier breeds due to potential genetic predisposition for development of pulmonary fibrosis.

Do not use in dogs that are pregnant, lactating, or intended for breeding.

Rabacfosadine is cytotoxic and may cause birth defects and affect female and male fertility. TANOVEA has not been evaluated in pregnant, lactating, or breeding dogs.

WARNINGS:

USER SAFETY WARNINGS:

NOT FOR USE IN HUMANS. KEEP THIS AND ALL MEDICATIONS OUT OF THE REACH OF CHILDREN. Do not store near food or with medications intended for use in humans. Do not eat, drink, or smoke while handling the product.

CHILDREN SHOULD NOT COME INTO CONTACT WITH TANOVEA. Children should not come into contact with feces, urine, vomit, and saliva of treated dogs for 5 days after each treatment.

Drug Handling and Administration

Pregnant women, women who may become pregnant, and nursing women should not handle, prepare, or administer TANOVEA. Rabacfosadine is cytotoxic and may cause birth defects and affect female and male fertility.

Use standard measures for the safe handling of all chemotherapeutic drugs. Refer to Occupational Safety and Health Administration (OSHA) for appropriate guidelines, recommendations, and regulations for handling antineoplastic agents.

Do not come into direct contact with TANOVEA. Wear chemotherapy-resistant gloves, goggles, and protective clothing when handling or administering TANOVEA. After removing and disposal of gloves, wash hands immediately and thoroughly with soap and water.

Accidental Exposure to TANOVEA

In the case of accidental self-injection:

- Remove glove.
- Let the wound bleed a few drops of blood.
- Rinse the wound thoroughly with tap water.
- Seek medical advice immediately and show the package insert, label, or client information sheet to the physician.

In case of accidental skin contact:

- Wash the affected area immediately and thoroughly with soap and water.

In the case of accidental eye exposure:

- Remove contact lenses.
- Rinse the eyes with large amounts of tap water (use eyewash station if present) for 10 minutes while holding back the eyelid.
- Seek medical advice immediately and show the package insert, label, or client information sheet to the physician.

In the case of accidental ingestion:

- Seek medical advice immediately and show the package insert, label, or client information sheet to the physician.

Handling of Excreta and Soiled Items

Do not come into direct contact with the treated dog's feces, urine, vomit, and saliva for 5 days after each treatment with TANOVEA.

When cleaning up feces, urine, vomit, and saliva, wear disposable chemotherapy-resistant gloves to collect the contaminated substances with disposable absorptive material (such as paper towels) and place them into a plastic bag. Carefully remove the gloves and place them in the bag, and tie or fasten it securely before general disposal. Wash hands immediately and thoroughly with soap and water afterwards.

Do not wash any items soiled with feces, urine, vomit, and saliva from the dog for 5 days after each treatment with other laundry.

Wear disposable chemotherapy-resistant gloves when handling the dog's toys, food bowl, and water bowl. Wash food and water bowls separately from other items for 5 days after each treatment.

Accidental Exposure to Excreta

In the case of direct skin contact with feces, urine, vomit, and saliva of dogs for 5 days after each treatment:

- Wash the affected skin immediately and thoroughly with soap and water.

ANIMAL SAFETY WARNINGS:

TANOVEA is associated with life-threatening or fatal pulmonary fibrosis. The pulmonary fibrosis may be an idiosyncratic toxicity. Monitoring for signs of pulmonary dysfunction is recommended (see ADVERSE REACTIONS).

PRECAUTIONS:

TANOVEA is associated with dermatopathies (e.g., otitis, alopecia, dermatitis, erythema, pruritus, hyperpigmentation, skin ulcerations, and bacterial skin infections) which can worsen with subsequent treatment (see ADVERSE REACTIONS). Careful monitoring for changes in the skin and ears is recommended. Dose reductions and/or dose delays should be considered to mitigate dermatologic adverse reactions.

TANOVEA can cause neutropenia with a nadir around seven days post-treatment. Dogs should be frequently monitored for evidence of neutropenia during treatment with TANOVEA (see ADVERSE REACTIONS and TARGET ANIMAL SAFETY).

Extravasation of TANOVEA may cause pain and/or tissue injury. If extravasation is suspected, discontinue infusion immediately. Monitor the site for evidence of injury; consider local and systemic treatment measures as needed.

The safety and effectiveness of TANOVEA has not been evaluated in conjunction with other chemotherapeutic agents or other modalities for the treatment of lymphoma.

The effect of concomitant medications on the metabolism of TANOVEA has not been evaluated.

ADVERSE REACTIONS:

A randomized, placebo-controlled, masked, multicenter clinical field study evaluated the effectiveness and safety of TANOVEA for the treatment of lymphoma. One-hundred and twenty dogs received TANOVEA at a dose of 1 mg/kg, administered as a 30-minute intravenous infusion once every three weeks for one to five doses. Thirty-eight dogs received a placebo (saline) infusion.

The Veterinary Cooperative Oncology Group - common terminology criteria for adverse events (VCOG-CTCAE)^1 definitions were used to grade the adverse reactions observed: Grade 1 (mild), Grade 2 (moderate), Grade 3 (severe), Grade 4 (life-threatening), and Grade 5 (death or euthanasia). Most adverse reactions were Grade 1 or 2. The adverse reactions observed in the study and number of dogs experiencing each adverse reaction is summarized in Table 2 below.

The most common adverse reactions included diarrhea, decreased appetite, vomiting, lethargy, weight loss, and neutropenia. Though diarrhea, decreased appetite, vomiting, lethargy, and weight loss were observed in both groups, the incidence was higher in the TANOVEA group and there were more Grade 2 and 3 adverse reactions compared to the Placebo group.

Table 2. Adverse Reactions Reported During the Field Study
 | TANOVEA (n=120) |  | Placebo (n=38)
 | n | % | n | %
Diarrhea | 105 | 87.5 | 19 | 50
Decreased appetite | 82 | 68.3 | 15 | 39.5
Emesis | 82 | 68.3 | 9 | 23.7
Lethargy | 76 | 63.3 | 24 | 63.2
Weight loss | 58 | 48.3 | 4 | 10.5
Neutropeniaa | 55 | 45.8 | 0
Polydipsia | 40 | 33.3 | 6 | 15.8
Anorexia | 34 | 28.3 | 7 | 18.4
Otitisb | 31 | 25.8 | 0
Alopecia | 30 | 25 | 2 | 5.3
Adipsia | 29 | 24.2 | 5 | 13.2
Polyuria | 29 | 24.2 | 2 | 5.3
Dermatitis | 25 | 20.8 | 0
Increased appetite | 24 | 20 | 6 | 15.8
Hypoalbuminemia | 24 | 20 | 5 | 13.2
Anemia | 20 | 16.7 | 3 | 7.9
Hematochezia | 20 | 16.7 | 0
Dehydration | 17 | 14.2 | 1 | 2.6
Nausea | 15 | 12.5 | 2 | 5.3
Erythema | 15 | 12.5 | 1 | 2.6
Pruritus | 15 | 12.5 | 1 | 2.6
Hyperpigmentation | 14 | 11.7 | 0
Leukopenia | 14 | 11.7 | 0
Monocytosis | 13 | 10.8 | 3 | 7.9
Elevated alanine aminotransferase (ALT) | 13 | 10.8 | 2 | 5.3
Proteinuria | 13 | 10.8 | 2 | 5.3
Pulmonary disorderc | 13 | 10.8 | 0
Elevated creatine-kinase (CK) | 12 | 10 | 1 | 2.6
Oliguria | 12 | 10 | 1 | 2.6
Urinary tract infection | 12 | 10 | 1 | 2.6
Cough | 11 | 9.2 | 3 | 7.9
Increased blood urea nitrogen (BUN) or creatinine | 11 | 9.2 | 2 | 5.3
Elevated aspartate aminotransferase (AST) | 11 | 9.2 | 0
Neutrophilia | 10 | 8.3 | 3 | 7.9
Hematuria | 10 | 8.3 | 1 | 2.6
Massd | 10 | 8.3 | 0
Hyperthermia | 9 | 7.5 | 4 | 10.5
Thrombocytopenia | 9 | 7.5 | 3 | 7.9
Elevated symmetrical dimethylarginine (SDMA) | 9 | 7.5 | 2 | 5.3
Hypocalcemia | 9 | 7.5 | 2 | 5.3
Glucosuriae | 9 | 7.5 | 0
Skin ulceration | 9 | 7.5 | 0
Tachypnea | 8 | 6.7 | 5 | 13.2
Dyspnea | 7 | 5.8 | 5 | 13.2
Elevated total bilirubin | 7 | 5.8 | 1 | 2.6
Hypokalemia | 7 | 5.8 | 1 | 2.6
Bacterial skin infection | 7 | 5.8 | 0
Desquamation | 7 | 5.8 | 0
Leukocytosis | 6 | 5 | 5 | 13.2
Pinnal irritation | 6 | 5 | 1 | 2.6
Digestive tract disorders NOSf | 6 | 5 | 0
Hypoproteinemia | 6 | 5 | 0
aMost neutropenias were Grade 1 or 2. However, eight instances of Grade 3 and three instances of Grade 4 neutropenia were reported. Neutropenia was reported seven days after treatment and returned to the normal range in all but two instances by the next cycle.
bRepresents combined terms of Otitis Externa and Otitis Not Otherwise Specified (NOS)
cPulmonary disorders included pulmonary fibrosis or possible pulmonary fibrosis (five dogs), pulmonary interstitial pattern (three dogs), pneumonia (three dogs), alveolar pattern on radiographs (two dogs), pneumomediastinum (one dog), pneumonitis (one dog), pulmonary infiltrates on radiographs (one dog). Some dogs were reported with more than one abnormality.
dMasses included skin and subcutaneous masses
eGlucosuria ranges from 1+ to 4+. In one dog, a 1+ ketonuria was reported at the same time as a 4+ glucosuria.
fDigestive tract disorders NOS included regurgitation (three dogs) and abnormal stool color (three dogs).

The type and frequency of reported adverse reactions did not vary greatly by cycle of TANOVEA treatment. A single cycle was the day of treatment and the 20 days after treatment (total of 21 days). However, during Cycles 1 and 2 (after the first or second dose), the majority of adverse reactions were primarily related to gastrointestinal and constitutional signs (i.e. lethargy, weight loss), while dermatopathies began to occur more frequently in Cycles 3 through 5 (after the third through fifth dose).

Serious Adverse Reactions

Serious adverse events (SAEs) were reported in 20% of dogs in the TANOVEA group (24 of 120 dogs) and 13% of dogs in the placebo group (five of 38 dogs). In the 24 TANOVEA dogs, SAEs included pulmonary fibrosis (five dogs) and dermatopathy (six dogs) as described below. Other SAEs included three cases of progressive disease (Grade 5), three cases of unrelated neoplasia/comorbidities, and one case each of hepatopathy (Grade 3), renal insufficiency (Grade 3), neutropenia (Grade 4), nausea (Grade 3), lymph node abscess (Grade 3), colitis (Grade 3), and hematochezia (Grade 3).

Pulmonary Fibrosis

Five dogs in the TANOVEA group developed severe adverse reactions associated with pulmonary fibrosis. The clinical signs included dyspnea, tachypnea, and orthopnea. Four of these dogs also had pneumomediastinum, pneumothorax, and/or emphysema diagnosed radiographically. All five dogs had radiographic findings that could be associated with pulmonary fibrosis along with accompanying pulmonary clinical signs. All five dogs were euthanized (four dogs) or died (one dog) due to the pulmonary fibrosis (either during the study or after removal from the study). Two of these dogs had a histologic confirmation of fibrosis on necropsy. The median time from randomization to first detection of clinical signs was 87 days (range 84 to 140) and the median time from randomization to death was 127 days (range 112 to 172). At the time of withdrawal (due to adverse reactions), all five dogs had a complete response to treatment. Pulmonary fibrosis may be an idiosyncratic adverse reaction with an unknown mechanism of action.

Dermatopathy

Over half of the patients (67/120 dogs) treated with TANOVEA experienced one or more dermatologic adverse reactions during their treatment. These adverse reactions were predominantly Grade 1 and primarily included otitis, alopecia, dermatitis, erythema, pruritus, hyperpigmentation, skin ulcerations, and bacterial skin infections.

Dermatologic adverse reactions typically presented by Cycle 3 (after the third dose), suggesting a cumulative effect of TANOVEA-associated dermatopathy. Dose reductions and dose delays were implemented to mitigate dermal adverse reactions. Six dogs in the TANOVEA group had Grade 3 or Grade 4 dermal adverse reactions which appeared in Cycle 2 (two dogs), Cycle 3 (three dogs), and Cycle 5 (one dog). Grade 3 adverse reactions included bacterial skin infections, skin ulcerations, desquamation, and dermatitis. Grade 4 adverse reactions included skin ulceration (severe erythema and ulceration of skin on limbs, ventrum, and foot pads) and desquamation (moist desquamation along the inguinal region and encompassing perivulvar area).

Euthanasia

Nine dogs in the TANOVEA group (8%) and two dogs in the placebo group (5%) were euthanized while on study. Reasons for euthanasia included four cases of progressive lymphoma (one with multiple comorbidities and pre-existing dermatopathy), two cases of pulmonary fibrosis, one case of probable hemangiosarcoma, one case of pyelonephritis/renal failure, and one case was unspecified. An additional three dogs died/were euthanized after withdrawal from the study due to suspected pulmonary fibrosis. One dog was euthanized after withdrawal from the study due to sepsis secondary to dermatopathy.

Dose Reductions and Dose Delays

Twenty-nine dogs in the TANOVEA group dogs received dose reductions (from 1 to 0.8 mg/kg), which were typically employed on the second to fourth dose of TANOVEA. Four dogs received a second stepwise reduction (from 0.8 to 0.66 mg/kg), which were employed on the third to fifth dose. The primary reason for dose reduction was gastrointestinal toxicity (diarrhea, vomiting, nausea), followed by dermatopathies, weight loss, anorexia/hyporexia, neutropenia, thrombocytopenia, and hypoalbuminemia. All dogs continued on the reduced dose(s) for the remainder of the study or until withdrawn.

Fourteen dogs in the TANOVEA group had a dose delay, which typically was one week beyond the intended treatment day. The primary reason cited in all cases was dermatopathy, and one case also cited weight loss. Eight dogs had both a dose reduction and delay, primarily attributable to dermatopathies.

Infusion Site Observations

On the day of treatment, two incidences of bruising were reported in dogs in the TANOVEA group. Infusion site observations seven days after treatment in dogs in the TANOVEA group included pigmentation (seven incidences), scaling (five incidences), erythema (three incidences), and swelling (two incidences).

Conditional Approval Experience:

Rabacfosadine for injection was conditionally approved and marketed from 2016-2021 under the proprietary name TANOVEA-CA1. The adverse events voluntarily reported for TANOVEA-CA1 (i.e., reports not associated with the clinical study) were similar to those described in the ADVERSE REACTIONS section above.

CONTACT INFORMATION:

To report suspected adverse events, for technical assistance, or to obtain a copy of the Safety Data Sheet, contact Elanco US Inc. at 1-877-468-3832.

For additional information about adverse drug experience reporting for animal drugs, contact FDA at 1-888-FDA-VETS or http://www.fda.gov/reportanimalae.

INFORMATION FOR DOG OWNERS:

Always provide the Client Information Sheet and review it with the dog owner or person responsible for care of the dog. Advise dog owners about possible adverse reactions, when to contact a veterinarian, and how to clean up any feces, urine, vomit, or saliva from dogs treated with TANOVEA. The Client Information Sheet also contains warnings for humans and what to do in case of accidental human exposure to TANOVEA.

CLINICAL PHARMACOLOGY:

Rabacfosadine is a prodrug of 9-(2-phosphonylmethoxyethyl)-N6-cyclopropyl-2, 6-diaminopurine (cPrPMEDAP) and 9-(2-phosphonylmethoxyethyl) guanine (PMEG). Rabacfosadine is hydrolyzed intracellularly to cPrPMEDAP and subsequently deaminated to PMEG. PMEG is then converted to its active phosphorylated form, PMEG diphosphate (PMEGpp), which is a potent, chain-terminating inhibitor of the major nuclear, replicative deoxyribonucleic acid (DNA) polymerases. The two prodrug moieties present in rabacfosadine increase the permeability and accumulation of metabolites in various cell types including peripheral blood mononuclear cells (PBMCs).

In vitro rabacfosadine has been demonstrated to inhibit DNA synthesis, resulting in S phase arrest and induction of apoptosis. Also in vitro rabacfosadine inhibits the proliferation of mitogen-stimulated lymphocytes and lymphoma/leukemia cell lines.

The in vivo data from studies in healthy dogs and dogs with lymphoma illustrated rapid clearance of rabacfosadine following a 30-minute intravenous infusion resulting in plasma exposure to the metabolite cPrPMEDAP and undetectable levels of the generally more cytotoxic agent PMEG. The exposure of rabacfosadine and cPrPMEDAP was linear with no gender differences. The mean peak plasma concentrations (Cmax) for rabacfosadine and cPrPMEDAP occurred at approximately 30 minutes (Tmax) and 1-2 hours, respectively. In dogs with lymphoma, rabacfosadine and cPrPMEDAP had a plasma half-life of <0.5 hour and 6 hours, respectively. In contrast to plasma, high concentrations of PMEG were readily detectable in PBMCs. Following rabacfosadine administration at 0.82 mg/kg over 30 minutes by intravenous infusion (once every two or three weeks), cPrPMEDAP and PMEGpp concentrations in lymphoid cells and tissues (represented by PBMCs) were 131 and 1,420 nM, respectively. In lymphoid cells, high concentrations of the active metabolite PMEGpp accumulated and persisted for greater than 24 hours. In PBMCs, the metabolites cPrPMEDAP and PMEGpp showed a terminal half-life of 25 hours and 68.7 hours, respectively. The observed PMEGpp concentrations in lymphoid cells and tissues are sufficient to allow for the desired antiproliferative effect following a single intravenous infusion administered once every three weeks.

Following intravenous administration of [^14C]-rabacfosadine to dogs, the excretion of radiolabeled material was similar in both feces and urine accounting for 42.4% and 32.5% of the dose, respectively, at 120 hours.

By 24 hours, radioactivity was widely distributed throughout the body. Some of the highest concentrations in tissues observed, with the exception of excretory organs, were found in lymphoid tissues. The mean overall elimination of radioactivity after intravenous dosing was 79.7% over 120 hours.

Approximately 10% of the administered dose was retained in tissues. The overall mass balance including radioactivity retained in the tissues would be estimated to be a mean of 88.8%. No central nervous system penetration was observed.

While the cytotoxic agent PMEG has been observed in PBMCs, PMEG was not observed in the liver, kidney, bile, or urine following administration of [14C]-rabacfosadine to dogs. Because the effective clinical plasma concentration is anticipated to be <2 μM and rabacfosadine is a prodrug that has a short half-life in dogs, rabacfosadine is unlikely to be a clinically relevant inhibitor or inducer of the major CYP450 pathways.

EFFECTIVENESS:

The effectiveness and safety of TANOVEA (rabacfosadine for injection) for the treatment of lymphoma was evaluated in a randomized, placebo-controlled, masked, multicenter clinical field study. TANOVEA was compared to placebo (saline) using progression free survival (PFS) as the primary endpoint. PFS was defined as the interval between the date of randomization and the first date that criteria for progressive disease were met, or the date of death, whichever occurred first. Response assessments were made according to the Veterinary Cooperative Oncology Group Response Evaluation Criteria for Peripheral Nodal Lymphoma in Dogs.^2 The study enrolled dogs of any breed, except West Highland White Terrier, or any sex diagnosed with multicentric lymphoma with at least one measurable peripheral lymph node.

One hundred and fifty-eight dogs were randomly assigned to treatment with either 1 mg/kg TANOVEA (n=120) or placebo (n=38) as a 30-minute intravenous infusion, once every three weeks for five doses, or until disease progression or withdrawal from the study for another cause. Dose delays of up to 14 days or stepwise dose reductions to 0.8 mg/kg and 0.66 mg/kg were allowed to manage adverse reactions. Effectiveness was evaluated in 148 dogs (112 in the TANOVEA group and 36 in the placebo control group).

The effectiveness analysis demonstrated a statistically significantly longer median PFS (P <0.0001) in dogs administered TANOVEA compared to placebo (82 days vs. 21 days, respectively).

The median PFS was 151 days in dogs in the TANOVEA group that exhibited a partial response (PR) or complete response (CR) and 168 days for dogs with a CR. The best overall response rate (BORR; the percent of dogs with a PR or CR as their highest response on study) was 73.2% (82/112 dogs) for dogs in the TANOVEA group (50.9% CR; 57/112 dogs) vs. 5.6% (2/36 dogs) for dogs in the placebo group (0% CR; 0/36 dogs).

For dogs with B-cell lymphoma, the median PFS was greater for dogs in the TANOVEA group compared to dogs in the placebo group (126 vs. 21 days, respectively). A smaller trend was observed for dogs with T-cell lymphoma (29 vs. 17 days, respectively). In the TANOVEA group, the BORR was 80.4% (74/92 dogs) in dogs with B-cell lymphoma (58.7% CR; 54/92 dogs), and 40.0% (8/20 dogs) in dogs with T-cell lymphoma (15.0% CR; 3/20 dogs).

For dogs naïve to prior chemotherapy regimens, the median PFS was greater for dogs in the TANOVEA group compared to dogs in the placebo group (143 vs. 19 days, respectively), with a shorter duration of PFS observed for dogs that had received prior chemotherapy (63 vs. 21 days, respectively). Dogs in the TANOVEA group with one prior chemotherapy had a median PFS of 82 days (127 days in dogs with a response to treatment). Dogs with B-cell lymphoma in the TANOVEA group with one prior chemotherapy regimen had a median PFS of 107 days (172 days in dogs with a response to treatment). Dogs with T-cell lymphoma in the TANOVEA group with one prior chemotherapy regimen had a median PFS of 21 days.

The BORR in dogs in the TANOVEA group were impacted by the number of prior chemotherapy regimens, with a BORR of 88.7% (47/53 dogs) in naïve dogs (62.3% CR; 33/53 dogs), 70.3% (26/37 dogs) in dogs with one prior chemotherapy regimen (54.1% CR; 20/37 dogs), and 40.9% (9/22 dogs) in dogs with more than one prior chemotherapy regimen (18.2% CR; 4/22 dogs).

See Table 3 below for a response summary in TANOVEA treated dogs.

Table 3. Response Summary in TANOVEA-Treated Dogs
 | Overall | B-cell | T-cell | Naive | 1 prior a | >1 priora | 1 prior (B- cell)a | 1 prior (T- cell)a | >1 prior (B- cell)a | >1 prior (T- cell)a
n | 112 | 92 | 20 | 53 | 37 | 22 | 30 | 7 | 18 | 4
Median PFS (days) | 82 | 126 | 29 | 143 | 82 | 41 | 107 | 21 | 39 | 60
Median PFS (responding dogs) | 151 | 161 | 55 | 160 | 127 | 64 | 172 | N/Ab | 64 | N/Ac
Median PFS (CR only) | 168 | 168 | 63 | 168 | 172 | NEd | 172 | N/Ab | NEd | NOe
% BORR | 73.2 | 80.4 | 40 | 88.7 | 70.3 | 40.9 | 83.3 | 14.3 | 44.4 | 25
% CR (anytime) | 50.9 | 58.7 | 15 | 62.3 | 54.1 | 18.2 | 63.3 | 14.3 | 22.2 | 0
% PR (anytime) | 22.3 | 21.7 | 25 | 26.4 | 16.2 | 22.7 | 20 | 0 | 22.2 | 25
a Refers to number of prior chemotherapy regimens (e.g., 0, 1, >1)
b N/A: Not applicable. Includes one dog with a PFS of 43 days
c N/A: Not applicable. Includes one dog with a PFS of 60 days
d NE: Not estimable. Includes four dogs with PFS of 50, 63, 161, and 360 days
e NO: No observations

At the time of the Day 112 visit (one month after the last treatment), 33.0% (37/112 dogs) of dogs in the TANOVEA group were progression free compared with 0 (0/36 dogs) placebo dogs. Forty-four TANOVEA dogs completed five cycles of treatment, and five dogs had a CR at Day 365 (study end). Only one placebo dog completed five cycles and no placebo dogs achieved a CR. The primary reason for early withdrawal from the study for all dogs in both groups was disease progression, followed by death and adverse reactions.

Concomitant medications were used primarily for diarrhea, decreased appetite, and dermatopathy (bacterial skin infections). The most commonly used concomitant medications included antiemetics, antibiotics, electrolyte solutions, sedatives, appetite stimulants, analgesics, and topical corticosteroids with anti-infectives. No other chemotherapies or systemic corticosteroids were used in the study.

TARGET ANIMAL SAFETY:

The margin of safety and toxicity of rabacfosadine (not commercial formulation) was evaluated in three laboratory safety studies and one laboratory cardiovascular study. For each laboratory safety study, there were six male and six female, seven to eight month old Beagle dogs per treatment group. Three dogs/sex/group were necropsied following the last dose and three dogs/sex/group were necropsied following a 21-day recovery period. The VCOG-CTCAE^1 definitions were used to grade the adverse reactions observed.

In the first study, a single dose of rabacfosadine was administered by a 30-minute intravenous infusion at doses of 0 (5% dextrose for injection), 0.25, 0.82, 2.5, and 8.2 mg/kg. Doses up to 2.5 mg/kg were tolerated. There were no adverse signs in the dogs administered 0.25 mg/kg. One dog administered 0.82 mg/kg vomited once. Dogs administered 2.5 mg/kg had abnormal feces (black, green, liquid, red, soft, mucoid) beginning on Day 4 and resolving by Day 10, and vomiting. There was a dose dependent weight loss and decreased food consumption in dogs administered ≥0.82 mg/kg. In all groups, including control, there were dermatologic changes (fur loss, thin fur, dry skin, red skin, skin lesions, scabs); there appeared to be a higher incidence in the dogs administered 2.5 mg/kg. Hematological changes included dose dependent leukopenia and Grade 1 to 4 neutropenia in dogs administered ≥0.82 mg/kg, with the nadir occurring between Days 6 and 9 and recovery occurring by Day 12. The 8.2 mg/kg dose was not tolerated. Dogs administered 8.2 mg/kg had clinical signs of abnormal feces, dehydration, vomiting, salivation, fever, tremors, decreased activity, and weakness resulting in a moribund state, and were either preterminally found dead or euthanized by Day 7. On necropsy at Day 3, pathology changes included dose-dependent effects on the gastrointestinal tract, lymphoid tissue, bone marrow, prostate, adrenal cortex, and kidneys (see below for more details). Following a 21-day recovery period, the majority of the changes in the intestines and lymphoid tissues reversed. Dose-dependent effects on the kidney were still observed.

In the second study, rabacfosadine was administered by a 30-minute intravenous infusion at doses of 0 (5% dextrose for injection), 0.082, 0.25, and 0.82 mg/kg once daily for 5 consecutive days and was tolerated at all dose levels. Dogs administered 0.82 mg/kg/day had suspected dehydration, vomiting, abnormal feces (soft, liquid, green, red), anorexia/hyporexia, decreased activity, and fever. Dogs with suspected dehydration received Lactated Ringers Solution subcutaneously. Treatment-related body weight loss and decreased food consumption were observed in dogs administered ≥0.25 mg/kg/day. In all groups, including control, there were dermatologic changes (fur loss, thin fur, dry skin, red skin, skin lesions, and scabs); there appeared to be a higher incidence in the groups administered drug.

Hematological changes included dose dependent leukopenia in all treated groups and dose dependent Grade 1 to 4 neutropenia in dogs administered ≥0.25 mg/kg/day with nadirs occurring between Days 6 and 9 with recovery by Day 12. On necropsy at Day 6, pathology changes included dose-dependent effects on the gastrointestinal tract, lymphoid tissue, bone marrow, and male reproductive system (see below for more details). Following a 21-day recovery period, dose-dependent changes were present in the gastrointestinal tract, salivary gland, kidney, and testes in all treated dogs, in the pancreas and thymus in dogs administered ≥0.25 mg/kg/ day, and in the bone marrow in dogs administered 0.82 mg/kg/day.

In the third study, rabacfosadine was administered by a 30-minute intravenous infusion at doses of 0 (5% dextrose for injection), 0.25, 0.50, and 1.0 mg/kg once every 7 days for 3 doses was tolerated at all dose levels. Treatment-related body weight loss and decreased food consumption were observed in dogs administered 1.0 mg/kg. In all groups, including control, there were dermatologic changes (fur loss, thin fur, dry skin, red skin, skin lesions, scabs); there appeared to be a higher incidence in the groups administered drug. Hematological changes included Grade 1 neutropenia predominantly in dogs administered 1.0 mg/kg. On necropsy on Day 16, pathology changes included dose-dependent effects on the gastrointestinal tract and lymphoid tissue, and non-dose dependent effects on the salivary gland, male reproductive tract, and kidney (see below for more details). These changes had only partial reversibility after a 21-day recovery period.

The pathology changes observed in the three studies included, in the gastrointestinal tract, necrosis of the stomach and combinations of mucosal hemorrhage, dilatation of mucosal glands/crypts, necrosis of crypt epithelial cells, atrophy of the mucosa/villi, edema, and inflammation of the intestinal wall. In the lymphoid tissue, observations included atrophy and necrosis of the thymus, spleen, lymph nodes, and gut associated lymphoid tissue (GALT). In the bone marrow, observations included hematopoietic hypocellularity. In the mandibular salivary gland, observations included glandular cell necrosis, atrophy, and inflammation. In the male reproductive tract, observations included small testes and epididymides, degeneration/atrophy of the seminiferous epithelium, and necrosis of the prostate. In the kidneys, observations included renal tubular vacuolation, dilatation, basophilia, degeneration, necrosis, and fibrosis. Tubular regeneration was observed following the recovery period. In the adrenal gland, observations included increased mitotic figures/necrosis in the adrenal cortex and adrenal fibrosis. In the pancreas, observations included acinar cell necrosis.

In the cardiovascular study, four telemeterized male, seven to eight month old Beagle dogs were administered 0 (5% dextrose for injection), 0.25, and 2.5 mg/kg rabacfosadine intravenously in an escalating dose regimen with a washout between doses. Dogs were monitored for 24 hours following dosing. There were no treatment-related effects on arterial blood pressure (mean, systolic, diastolic), heart rate, or electrocardiographic parameters.

STORAGE CONDITIONS:

Unopened vials: Store the vials refrigerated at 2 °C to 8 °C (36 °F to 46 °F). Retain in the original package to protect from light.

After reconstitution: Store at 20 °C to 25 °C (68 °F to 77 °F). TANOVEA should be diluted for infusion within 4 hours of reconstitution. The infusion solution should be used within 24 hours of being added to the infusion bag or syringe and within 4 hours of attachment to an intravenous administration set. Protection from light is not needed.

Disposal: Dispose of any unused product or waste materials in accordance with proper procedures for cytotoxic drugs.

HOW SUPPLIED:

TANOVEA is supplied in a 3 mL amber Type I glass vial with rubber stopper, aluminum over-seal, and plastic flip-off cap, packaged in a carton. Each vial contains 16.4 mg of rabacfosadine, as succinate salt.

Pack size: 4 vials and 10 vials

REFERENCES:

1. Veterinary Cooperative Oncology Group. Veterinary cooperative oncology group - common terminology criteria for adverse events (VCOG-CTCAE) following chemotherapy or biological antineoplastic therapy in dogs and cats v1.1. Veterinary and Comparative Oncology 2016;14(4):417-446.
2. Vail DM, et al. Response evaluation criteria for peripheral nodal lymphoma in dogs (v1.0)–a veterinary cooperative oncology group (VCOG) consensus document. Veterinary and Comparative Oncology 2009;8(1):28-37.

Manufactured for:

Elanco US Inc.

Greenfield, IN 46140

Product of Canada

Revision date: January 2022

Approved by FDA under NADA # 141-545

Tanovea, Elanco and the diagonal bar logo are trademarks of Elanco or its affiliates.

© 2022 Elanco or its affiliates

PA103455X

Principal Display Panel - 16.4 mg 10 Vials Carton Label

TANOVEA®

(rabacfosadine for injection)

Antineoplastic

For intravenous use in dogs

Elanco™

16.4 mg rabacfosadine
per vial

10 single-use vials

CAUTION: Federal law restricts this drug to use by or on
the order of a licensed veterinarian. Use only as directed.

INDICATION: For the treatment of lymphoma in dogs

Net contents: 10 single-use vials

Approved by FDA under NADA # 141-545

Principal Display Panel - 16.4 mg 4 Vials Carton Label

TANOVEA®

(rabacfosadine for injection]

Antineoplastic

For intravenous use in dogs

Elanco™

16.4 mg rabacfosadine
per vial

4 single-use vials

CAUTION: Federal law restricts this drug to use by or on
the order of a licensed veterinarian. Use only as directed.

INDICATION: For the treatment of lymphoma in dogs

Net contents: 4 single-use vials

Approved by FDA under NADA # 141-545